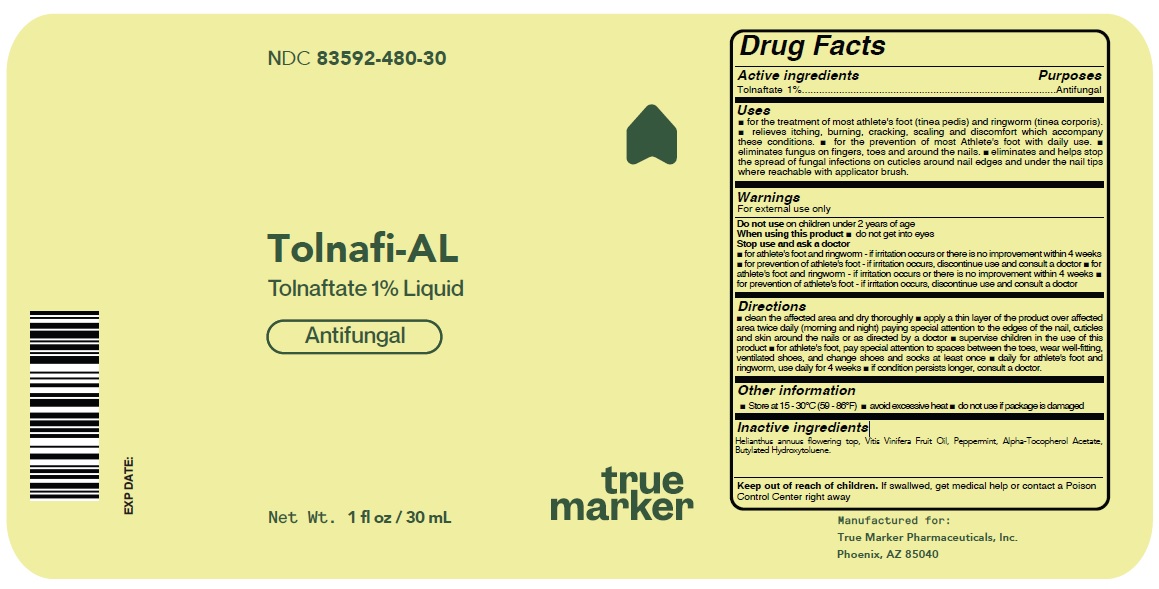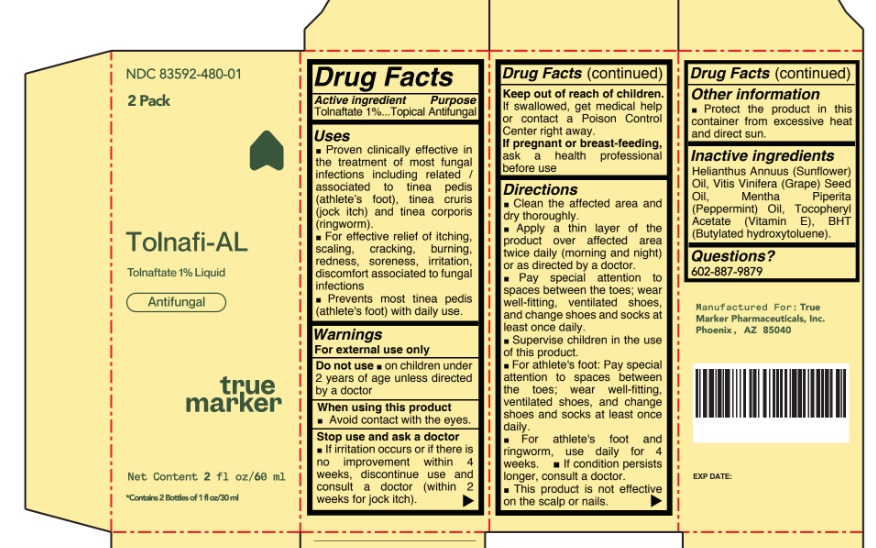 DRUG LABEL: Tolnafi-AL
NDC: 83592-480 | Form: LIQUID
Manufacturer: True Marker Pharmaceuticals, Inc.
Category: otc | Type: HUMAN OTC DRUG LABEL
Date: 20241007

ACTIVE INGREDIENTS: TOLNAFTATE 1 g/100 mL
INACTIVE INGREDIENTS: HELIANTHUS ANNUUS FLOWERING TOP; VITIS VINIFERA FRUIT OIL; PEPPERMINT; .ALPHA.-TOCOPHEROL ACETATE; BUTYLATED HYDROXYTOLUENE

Drug Facts

Active Ingredient (s)

Tolnaftate 1%

Purpose

Antifungal

Uses

• Proven clinically effective in the treatment of most fungal infections including related/associated to tinea pedis (athlete’s foot), tinea cruris (jock itch) and tinea corporis (ringworm)
• For effective relief of itching, scaling, cracking, burning, redness, soreness, irritation, discomfort associated to fungal infections
• Prevents most tinea pedis (athlete’s foot) with daily use.

Warnings

• For external use only
• Do Not Use– On children under 2 years of age unless directed by a doctor.
• When using this product, avoid contact with eyes.
• Stop use and ask a doctor

- for athlete's foot and ringworm - if irritation occurs or there is no improvement within 4 weeks
- for prevention of athlete's foot - if irritation occurs, discontinue use and consult a doctor
- for athlete's foot and ringworm - if irritation occurs or there is no improvement within 4 weeks
- for prevention of athlete's foot - if irritation occurs, discontinue use and consult a doctor

Inactive ingredients

If swallwed, get medical help or contact a Poison Control Center right away

Directions

- clean the affected area and dry thoroughly
- apply a thin layer of the product over affected area twice daily (morning and night) paying special attention to the edges of the nail, cuticles and skin around the nails or as directed by a doctor
- supervise children in the use of this product
- for athlete's foot, pay special attention to spaces between the toes, wear well-fitting,ventilated shoes, and change shoes and socks at least once
- daily for athlete's foot and ringworm, use daily for 4 weeks
- if condition persists longer, consult a doctor.

Other information

- Store at 15 - 30°C (59 - 86°F)
- avoid excessive heat
- do not use if package is damaged

Inactive Ingredients

Helianthus annuus flowering top, Vitis Vinifera Fruit Oil, Peppermint, Alpha-Tocopherol Acetate, Butylated Hydroxytoluene.